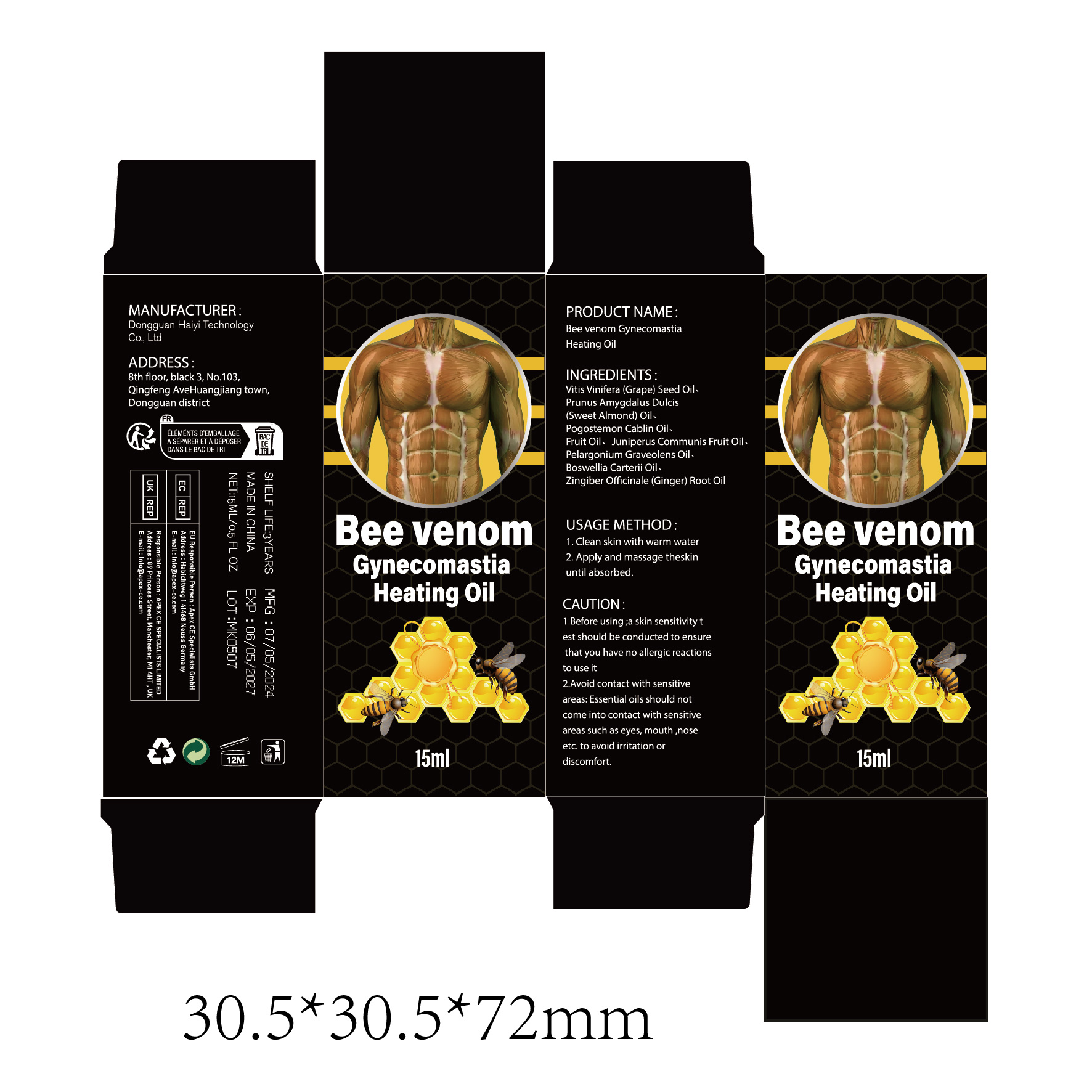 DRUG LABEL: Bee venom Gynecomastia Heating Oil
NDC: 84732-063 | Form: OIL
Manufacturer: Dongguan Haiyi Technology Co.,Ltd.
Category: otc | Type: HUMAN OTC DRUG LABEL
Date: 20241023

ACTIVE INGREDIENTS: GRAPE SEED OIL 1 mg/10 mL
INACTIVE INGREDIENTS: POGOSTEMON CABLIN LEAF OIL; ALMOND OIL; BOSWELLIA CARTERII OIL; GINGER OIL; GERANIUM OIL, ALGERIAN TYPE; JUNIPERUS COMMUNIS FRUIT OIL

Active ingredient

Vitis Vinifera (Grape) Seed Oil

Inactive ingredient

Prunus Amygdalus Dulcis(Sweet Almond) Oil、Pogostemon Cablin Oil、Fruit Oil、Juniperus Communis Fruit Oil、Pelargonium Graveolens Oil、Boswellia Carterii Oil、Zingiber Offcinale (Ginger) Root Oil

Purpose section

be to tighten the skin, reduce swelling

Warning

1.Before using ;a skin sensitivity test should be conducted to ensurethat you have no allergic reactionsto use it
2.Avoid contact with sensitiveareas: Essential oils should notcome into contact with sensitiveareas such as eyes, mouth ,noseetc. to avoid irritation ordiscomfort.

stop use

This product may cause allergic reactions in asmall number of people.
lf youexperience any discomfort,please stop using it immediately.

not use

Not suitable for use by children, pregnantor breast feeding people.

OUT OF CHILDREN

KEEP THE PRODUCT OUT OF REACH OF CHILDREN to

HOW TO USE

1.Clean skin with warm water

2. Apply and massage theskinuntil absorbed

Dosage

take an appropriateamount,Use 2-3 times a week